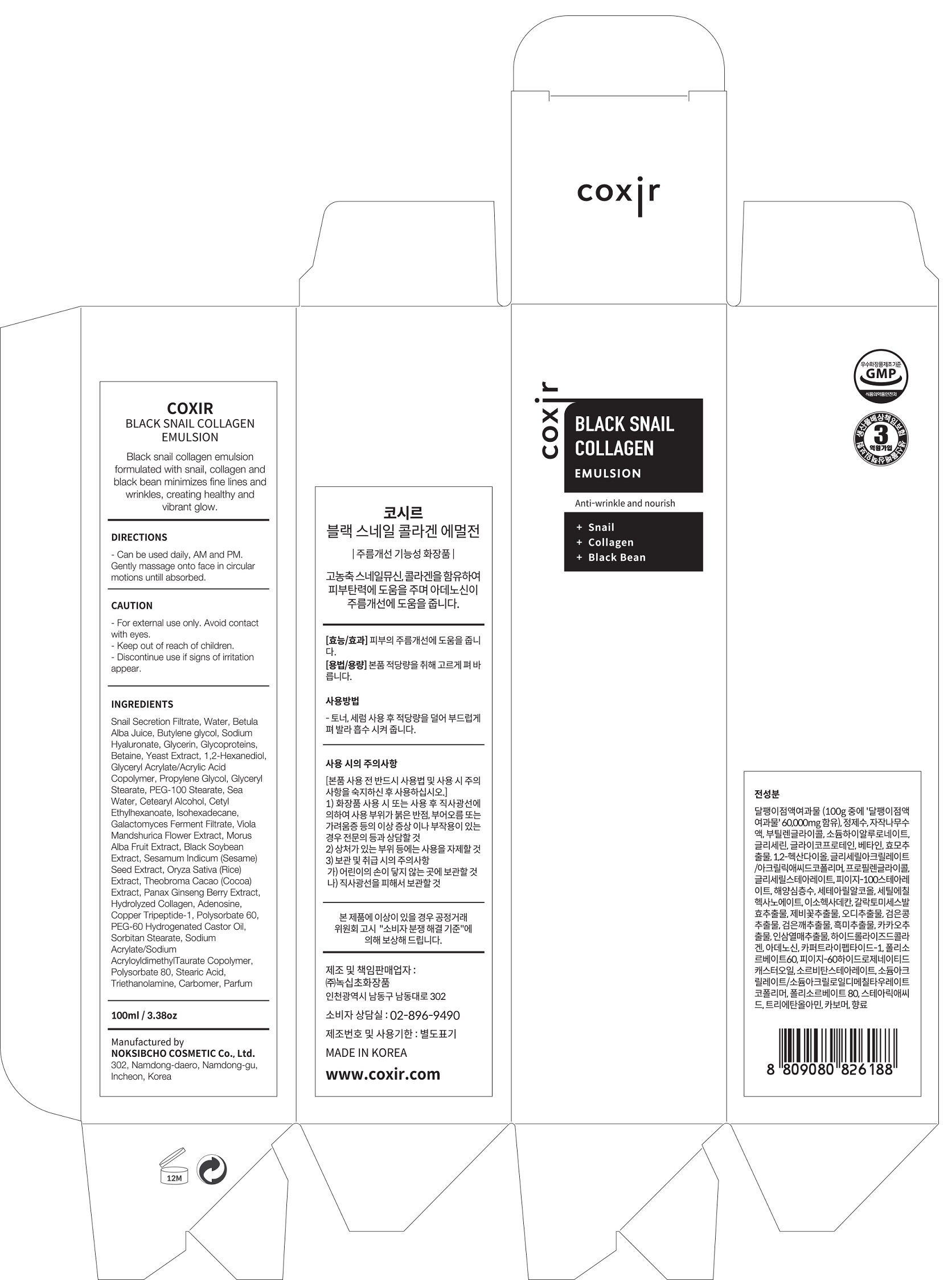 DRUG LABEL: Black Snail CollagenEmulsion
NDC: 73590-0012 | Form: EMULSION
Manufacturer: NOKSIBCHO cosmetic Co., Ltd.
Category: otc | Type: HUMAN OTC DRUG LABEL
Date: 20200314

ACTIVE INGREDIENTS: SNAIL, UNSPECIFIED 60 g/100 mL
INACTIVE INGREDIENTS: WATER; BUTYLENE GLYCOL

Drug Facts

ACTIVE INGREDIENT

Snail Secretion Filtrate

INACTIVE INGREDIENT

Water
Betula Alba Juice
Butylene glycol
Sodium Hyaluronate
Glycerin
Water
Glycoproteins
Sodium Hyaluronate
Betaine
1,3 Butylene glycol
Glycerin
1,2-Hexanediol
1,2-Hexanediol
Glyceryl Acrylate/Acrylic Acid Copolymer
Propylene Glycol
Glyceryl Stearate
PEG-100 Stearate
Sea Water
Cetearyl Alcohol
Cetyl Ethylhexanoate
Isohexadecane
Galactomyces Ferment Filtrate
Viola Mandshurica Flower Extract
Morus Alba Fruit Extract
Black Soybean Extract
Sesamum Indicum (Sesame)
Seed Extract
Oryza Sativa (Rice) Extract
Panax Ginseng Berry Extract
Hydrolyzed Collagen
Adenosine
Copper Tripeptide-1
Theobroma Cacao (Cocoa) Extract
Polysorbate 60
Betaine
PEG-60 Hydrogenated Castor Oil
Sorbitan Stearate
Sodium Acrylate/Sodium AcryloyldimethylTaurate Copolymer
Isohexadecane
Polysorbate 80
Stearic Acid
Triethanolamine
Carbomer
Parfum

PURPOSE

anti-wrinkle and nourish

keep out of reach of the children

INDICATIONS AND USAGE

apply proper amount and gently massage

WARNINGS

For external use only
When using this product

■ if the following symptoms occurs after use, stop use and consult with a skin specialist

red specks, swelling, itching

■ don’t use on the part where there is injury, eczema, or dermatitis

Keep out of reach of children

■ if swallowed, get medical help or contact a person control center immediately

DOSAGE AND ADMINISTRATION

for external use only